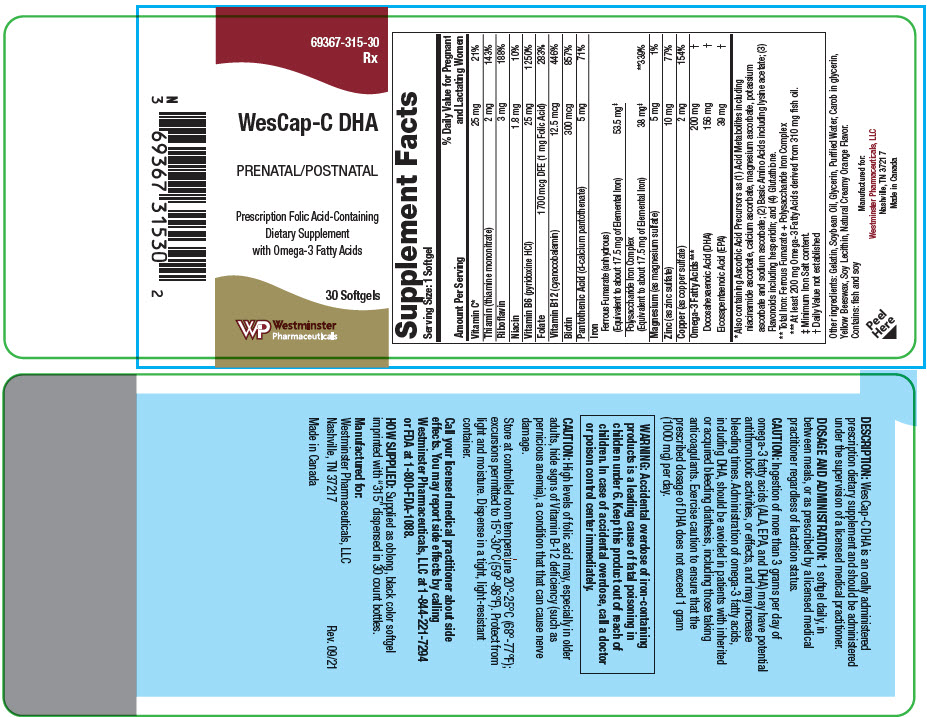 DRUG LABEL: WesCap-C-DHA
NDC: 69367-315 | Form: CAPSULE, GELATIN COATED
Manufacturer: Westminster Pharmaceuticals, LLC
Category: other | Type: DIETARY SUPPLEMENT
Date: 20250820

ACTIVE INGREDIENTS: ASCORBIC ACID 25 mg/1 1; THIAMINE MONONITRATE 2 mg/1 1; RIBOFLAVIN 3 mg/1 1; NIACIN 1.8 mg/1 1; PYRIDOXINE HYDROCHLORIDE 25 mg/1 1; FOLIC ACID 1 mg/1 1; CYANOCOBALAMIN 12.5 ug/1 1; BIOTIN 300 ug/1 1; CALCIUM PANTOTHENATE 5 mg/1 1; FERROUS FUMARATE 53.5 mg/1 1; IRON 38 mg/1 1; MAGNESIUM SULFATE, UNSPECIFIED FORM 5 mg/1 1; ZINC SULFATE, UNSPECIFIED FORM 10 mg/1 1; CUPRIC SULFATE 2 mg/1 1; DOCONEXENT 156 mg/1 1; ICOSAPENT 39 mg/1 1
INACTIVE INGREDIENTS: GELATIN, UNSPECIFIED; SOYBEAN OIL; WATER; GLYCERIN; YELLOW WAX; SOYBEAN LECITHIN

WesCap-C-DHA

STATEMENT OF IDENTITY

Supplement Facts
Serving Size: 1 Softgel
Amount Per Serving | % Daily Value for Pregnant and Lactating Women
Vitamin C [Also containing Ascorbic Acid Precursors as (1) Acid Metabolites including niacinamide ascorbate, calcium ascorbate, magnesium ascorbate, potassium ascorbate and sodium ascorbate; (2) Basic Amino Acids including lysine acetate; (3) Flavonoids including hesperidin; and (4) Glutathione.] | 25 mg | 21%
Thiamin (thiamine mononitrate) | 2 mg | 143%
Riboflavin | 3 mg | 188%
Niacin | 1.8 mg | 10%
Vitamin B6 (pyridoxine HCl) | 25 mg | 1250%
Folate | 1700 mcg DFE (1 mg Folic Acid) | 283%
Vitamin B12 (cyanocobalamin) | 12.5 mcg | 446%
Biotin | 300 mcg | 857%
Pantothenic Acid (d-calcium pantothenate) | 5 mg | 71%
Iron
Ferrous Fumarate (anhydrous)
(Equivalent to about 17.5 mg of Elemental Iron) | 53.5 mg [Minimum Iron Salt content.]
Polysaccharide Iron Complex
(Equivalent to about 17.5 mg of Elemental Iron) | 38 mg | [Total Iron: Ferrous Fumarate + Polysaccharide Iron Complex] 339%
Magnesium (as magnesium sulfate) | 5 mg | 1%
Zinc (as zinc sulfate) | 10 mg | 77%
Copper (as copper sulfate) | 2 mg | 154%
Omega-3 Fatty Acids [At least 200 mg Omega-3 Fatty Acids derived from 310 mg fish oil.] | 200 mg | [Daily Value not established]
Docosahexaenoic Acid (DHA) | 156 mg
Eicosapentaenoic Acid (EPA) | 39 mg

Other ingredients: Gelatin, Soybean Oil, Glycerin, Purified Water, Carob in glycerin, Yellow Beeswax, Soy Lecithin, Natural Creamy Orange Flavor.

Contains: fish and soy

DESCRIPTION

WesCap-C DHA is an orally administered prescription dietary supplement and should be administered under the supervision of a licensed medical practitioner.

DOSAGE AND ADMINISTRATION

1 softgel daily, in between meals, or as prescribed by a licensed medical practitioner regardless of lactation status.

CAUTION

Ingestion of more than 3 grams per day of omega-3 fatty acids (ALA, EPA, and DHA) may have potential antithrombotic activities, or effects, and may increase bleeding times. Administration of omega-3 fatty acids, including DHA, should be avoided in patients with inherited or acquired bleeding diathesis, including those taking anticoagulants. Exercise caution to ensure that the prescribed dosage of DHA does not exceed 1 gram (1000 mg) per day.

WARNINGS

WARNING: Accidental overdose of iron-containing products is a leading cause of fatal poisoning in children under 6. Keep this product out of reach of children. In case of accidental overdose, call a doctor or poison control center immediately.

CAUTION

High levels of folic acid may, especially in older adults, hide signs of Vitamin B-12 deficiency (such as pernicious anemia), a condition that that can cause nerve damage.

HEALTH CLAIM

Store at controlled room temperature 20°-25°C (68°-77°F); excursions permitted to 15°-30°C (59°-86°F). Protect from light and moisture. Dispense in a tight, light-resistant container.

Call your licensed medical practitioner about side effects. You may report side effects by calling Westminster Pharmaceuticals, LLC at 1-844-221-7294 or FDA at 1-800-FDA-1088.

HOW SUPPLIED

Supplied as oblong, black color softgel imprinted with "315" dispensed in 30 count bottles.

HEALTH CLAIM

Manufactured for:
Westminster Pharmaceuticals, LLC
Nashville, TN 37217

Rev. 09/21

Made in Canada

PRINCIPAL DISPLAY PANEL - 30 Softgel Bottle Label

69367-315-30
Rx

WesCap-C DHA

PRENATAL/POSTNATAL

Prescription Folic Acid-Containing
Dietary Supplement
with Omega-3 Fatty Acids

30 Softgels

Westminster
Pharmaceuticals